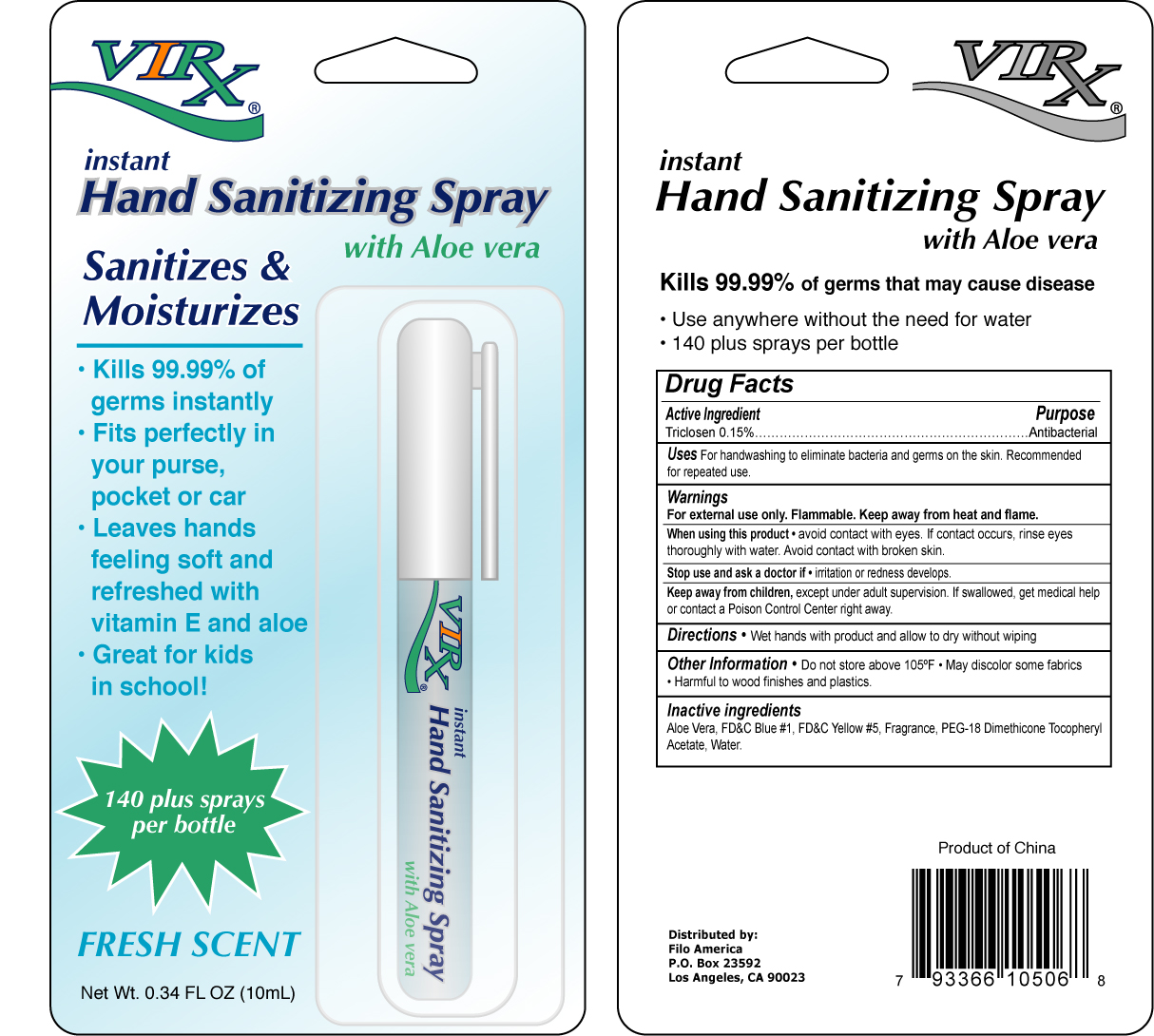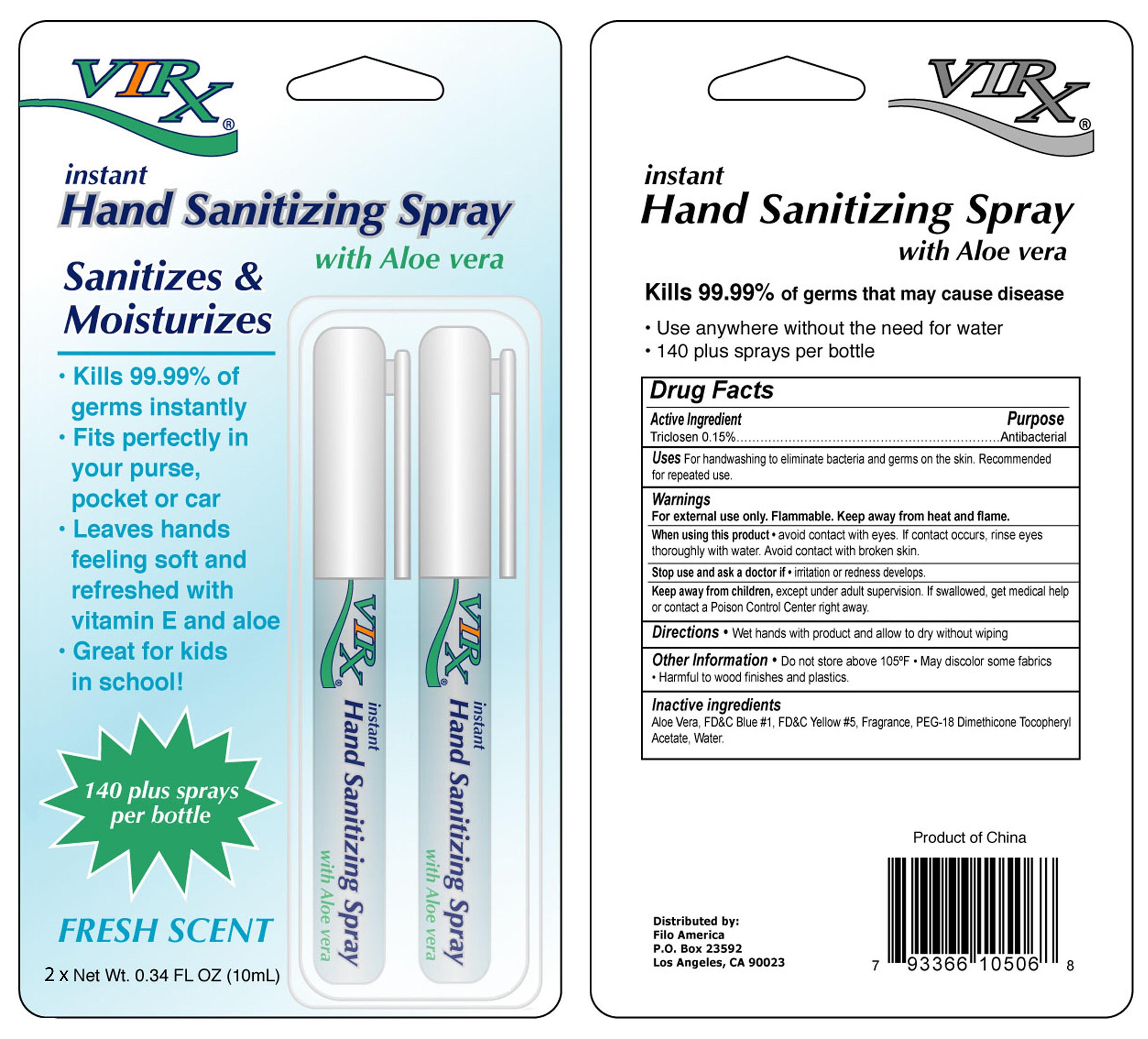 DRUG LABEL: Virx
NDC: 40104-556 | Form: SPRAY
Manufacturer: Ningbo Pulisi Daily Chemical Products Co., Ltd
Category: otc | Type: HUMAN OTC DRUG LABEL
Date: 20091123

ACTIVE INGREDIENTS: Triclosan 1.2 mL/10 mL
INACTIVE INGREDIENTS: Aloe Vera Leaf; FD&C Blue No. 1; FD&C Yellow No. 5; Dimethicone; Alpha-Tocopherol Acetate; Water

Virx Hand Sanitizing Spray with Aloe Vera

Drug Facts

Triclosan 0.15%...........................................................Antibacterial

Uses

For handwashing to eliminate bacteria and germs on the hand. Recommended for repeated use.

WARNINGS

For external use only. Flammable. Keep away from heat and flame.

When using this product avoid contact with eyes. If contact occurs, rinse eyes thoroughly with water. Avoid contact with broken skin.

Stop use and ask a doctor if irritation or redness develops.

KEEP OUT OF REACH OF CHILDREN

Keep away from children, except under adult supervision. If swallowed, get medical help or contact a Poison Control Center right away.

INDICATIONS AND USAGE

Wet hands with product and allow to dry without wiping.

GENERAL PRECAUTIONS

Do not store above 105 degrees. May discolor some fabrics. Harmful to wood finishes and plastics.

PACKAGE LABEL

MM1
MM2